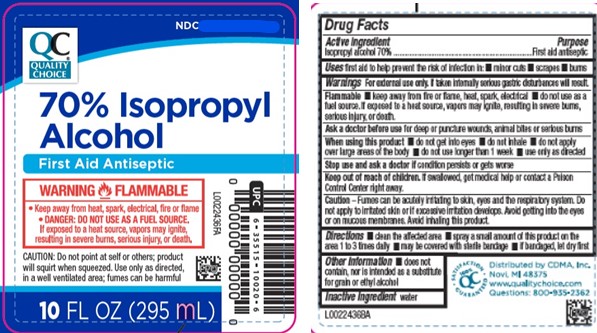 DRUG LABEL: 70% Isopropyl Alcohol
NDC: 83324-172 | Form: LIQUID
Manufacturer: Chain Drug Marketing Association
Category: otc | Type: HUMAN OTC DRUG LABEL
Date: 20260227

ACTIVE INGREDIENTS: ISOPROPYL ALCOHOL 70 mL/100 mL
INACTIVE INGREDIENTS: WATER

Quality Choice 810.003/810AA
70% Isopropyl Alcohol

Active ingredient

Isopropyl alcohol 70%

Purpose

First Aid Antiseptic

Uses

First aid to help prevent the risk of infection in:

- minor cuts
- scrapes
- burns

Warnings

For external use only. If taken internally serious gastric disturbances will result.

Flammable

- Keep away from fire or flame, heat, spark, electrical
- do not use as fuel source. If exposed to a heat source, vapors may ignite, resulting in severe burns, serious injury, or death.

Ask a doctor before use

for deep or puncture wounds, animal bites or serious burns

When using this product

- do not get into eyes
- do not inhale
- do not apply over large area of the body
- do not use longer than 1 week
- use only as directed

Stop use and ask a doctor if

condition persists or gets worse

Keep out of reach of children.

If swallowed, get medical hep or contact a Poison Control Center right away.

Caution

Fumes can be acutely irritating to skin, eyes and the respiratory system. Do not apply to irritated skin or if excessive irritation develops. Avoid getting into the eyes or on mucous membranes. Avoid inhaling this product.

Directions

- clean the affected area
- spray a small amount of this product on the area 1 to 3 times daily
- may be covered with a sterile bandage
- if bandaged, let dry first

Other information

- does not contain, nor is intended as a substitute for grain or ethyl alcohol

Inactive ingredient

water

Adverse reaction

QC 100% Satisfaction Guaranteed

Distributed by CDMA, Inc.

Novi, MI 48375

www.qualitychoice.com

Questions: 800-935-2382

Principal display panel

NDC 83324-172-10

QC®

Quality Choice

70% Isopropyl Alcohol

First Aid Antiseptic

WARNING FLAMMABLE

- Keep away from heat, spark, electrical, fire or flame
- DANGER: DO NOT USE AS A FUEL SOURCE. If exposed to a heat source, vapors may ignite, resulting in severe burns, serious injury, or death.

CAUTION: Do not point at self or others; product will squirt when squeezed. Use only as directed, in a well ventilated area; fumes can be harmful

10 FL OZ (295 mL)